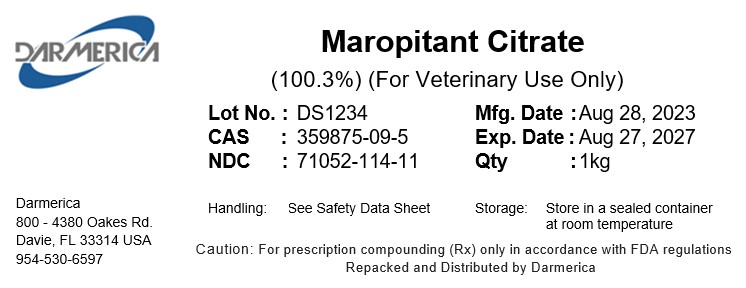 DRUG LABEL: Maropitant Citrate
NDC: 71052-114 | Form: POWDER
Manufacturer: DARMERICA, LLC
Category: other | Type: BULK INGREDIENT - ANIMAL DRUG
Date: 20240725

ACTIVE INGREDIENTS: Maropitant Citrate 1 kg/1 kg

Maropitant Citrate